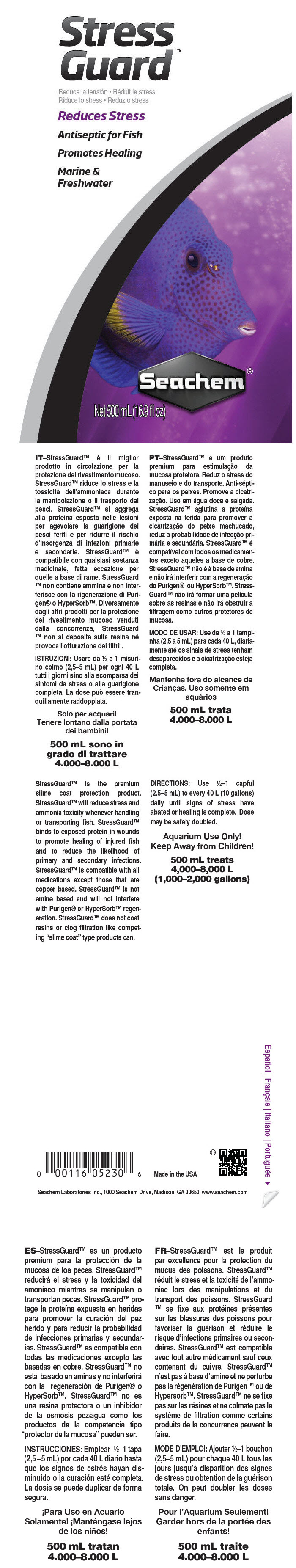 DRUG LABEL: Stressguard
NDC: 55999-053 | Form: LIQUID
Manufacturer: Seachem Laboratories Inc.
Category: animal | Type: OTC ANIMAL DRUG LABEL
Date: 20190807

ACTIVE INGREDIENTS: Glutaral 4 mg/1 mL; Methylene Blue 0.04 mg/1 mL

Stressguard™

StressGuard™ is the premium slime coat protection product. StressGuard™ will reduce stress and ammonia toxicity whenever handling or transporting fish. StressGuard™ binds to exposed protein in wounds to promote healing of injured fish and to reduce the likelihood of primary and secondary infections. StressGuard™ is compatible with all medications except those that are copper based. StressGuard™ is not amine based and will not interfere with Purigen® or HyperSorb™ regeneration. StressGuard™ does not coat resins or clog filtration like competing "slime coat" type products can.

DOSAGE AND ADMINISTRATION

DIRECTIONS: Use ½–1 capful (2.5–5 mL) to every 40 L (10 gallons) daily until signs of stress have abated or healing is complete. Dose may be safely doubled.

WARNINGS

Aquarium Use Only!
Keep Away from Children!

500 mL treats
4,000–8,000 L
(1,000–2,000 gallons)

Made in the USA

Seachem Laboratories Inc., 1000 Seachem Drive, Madison, GA 30650, www.seachem.com

PRINCIPAL DISPLAY PANEL - 500 mL Bottle Label

Stress
Guard™

Reduces Stress

Antiseptic for Fish

Promotes Healing

Marine &
Freshwater

Seachem®

Net 500 mL (16.9 fl oz)